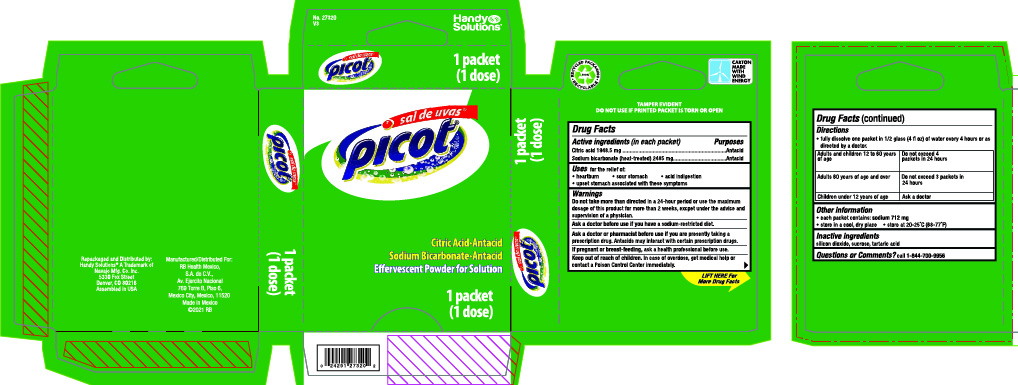 DRUG LABEL: Sal De Uvas Picot
NDC: 67751-174 | Form: GRANULE, EFFERVESCENT
Manufacturer: Navajo Manufacturing Company Inc.
Category: otc | Type: HUMAN OTC DRUG LABEL
Date: 20241002

ACTIVE INGREDIENTS: CITRIC ACID MONOHYDRATE 1.9485 g/1 1; SODIUM BICARBONATE 2.485 g/1 1
INACTIVE INGREDIENTS: SILICON DIOXIDE; SUCROSE; TARTARIC ACID

Sal De Uvas Picot

Active ingredients (in each packet)

Citric Acid 1948.5 mg
Sodium bicarbonate (heat-treated) 2485 mg

Purposes

Antacid

Uses

for the relief of:
• heartburn • sour stomach • acid indigestion
• upset stomach associated with these symptoms

Warnings

Do not take

more than directed in a 24-hour period or use the maximum dosage of this product for more than 2 weeks, except under the advice and supervision of a physician.

Ask a doctor before use if you have

a sodium-restricted diet.

Ask a doctor or pharmacist before use if you

are presently taking a prescription drug. Antacids may interact with certain prescription drugs.

If pregnant or breast-feeding,

ask a health professional before use.

Keep out of reach of children.

In case of overdose, get medical help or contact a Poison Control Center immediately.

Directions

- fully dissolve one packet in 1/2 glass (4 fl oz) of water every 4 hours or as directed by a doctor.

Adults and children 12 to 60 years of age | do not exceed 4 packets in 24 hours
Adults 60 years of age and over | do not exceed 3 packets in 24 hours
Children under 12 years of age | ask a doctor

Other information

- each packet contains: sodium 712 mg
- store in a cool, dry place
- store between 20-25°C (68-77°F)

Inactive ingredients

silicon dioxide, sucrose, tartaric acid

Questions or Comments?

call 1-844-700-9956

Package Labeling:

Made in Mexico

Manuf/Dist for:

RB Health Mexico

S.A. de C.V., Ejercito Nacional

769 Torre B, Piso 6,

Mexico City, Mexico, 11520